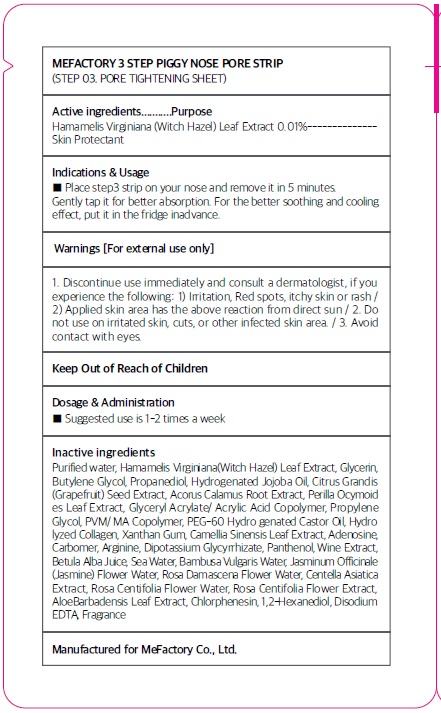 DRUG LABEL: Mefactory 3Step Piggy Nose Pore Strip Step 03 Pore Tightening Sheet
NDC: 70908-100 | Form: PATCH
Manufacturer: MeFactory Co., Ltd.
Category: otc | Type: HUMAN OTC DRUG LABEL
Date: 20170303

ACTIVE INGREDIENTS: Witch Hazel 0.3 mg/3 g
INACTIVE INGREDIENTS: WATER; Glycerin

ACTIVE INGREDIENT

Active ingredients: Hamamelis Virginiana (Witch Hazel) Leaf Extract 0.01%

INACTIVE INGREDIENT

Inactive ingredients: Purified water, Glycerin, Butylene Glycol ,Propanediol,Hydrogenated Jojoba Oil ,Citrus Grandis (Grapefruit) Seed Extract ,Acorus Calamus Root Extract,Perilla Ocymoides Leaf Extract ,Glyceryl Acrylate/Acrylic Acid Copolymer ,Propylene Glycol ,PVM/MA Copolymer ,PEG-60 Hydrogenated Castor Oil,Hydrolyzed Collagen,Xanthan Gum ,Camellia Sinensis Leaf Extract ,Adenosine,Carbomer ,Arginine,Dipotassium Glycyrrhizate ,Panthenol,Wine Extract ,Betula Alba Juice ,Sea Water,Bambusa Vulgaris Water,Jasminum Officinale (Jasmine) Flower Water ,Rosa Damascena Flower Water ,Centella Asiatica Extract ,Rosa Centifolia Flower Water ,Rosa Centifolia Flower Extract ,Aloe Barbadensis Leaf Extract ,Chlorphenesin ,1,2-Hexanediol ,Disodium EDTA ,Fragrance

PURPOSE

Purpose: Skin Protectant

WARNINGS

Warnings: For external use only 1. Discontinue use immediately and consult a dermatologist, if you experience the following: 1) Irritation, Red spots, itchy skin or rash 2) Applied skin area has the above reaction from direct sun 2. Do not use on irritated skin, cuts, or other infected skin area. 3. Avoid contact with eyes.

KEEP OUT OF REACH OF CHILDREN

INDICATIONS & USAGE

Indications & Usage: Place step3 strip on your nose and remove it in 5 minutes. Gently tap it for better absorption. For the better soothing and cooling effect, put it in the fridge in advance.

DOSAGE & ADMINISTRATION

Dosage & Administration: Suggested use is 1-2 times a week